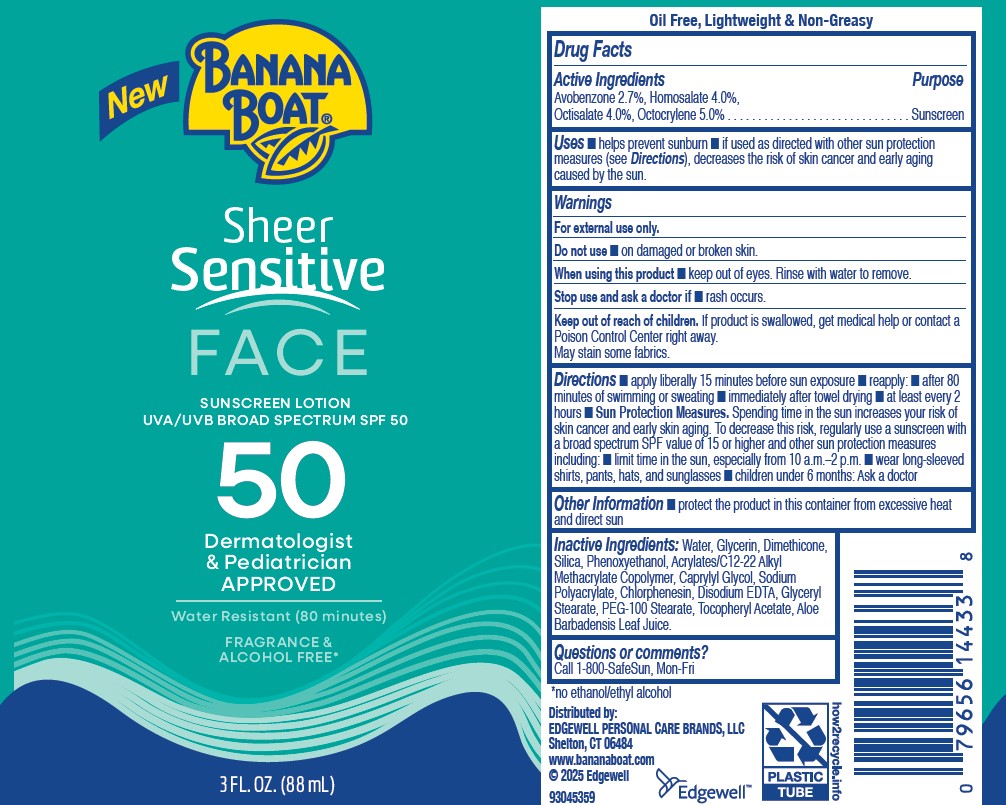 DRUG LABEL: BANANA BOAT
NDC: 63354-934 | Form: LOTION
Manufacturer: Edgewell Personal Care Brands LLC
Category: otc | Type: HUMAN OTC DRUG LABEL
Date: 20251202

ACTIVE INGREDIENTS: AVOBENZONE 2.7 g/100 g; OCTOCRYLENE 5 g/100 g; HOMOSALATE 4 g/100 g; OCTISALATE 4 g/100 g
INACTIVE INGREDIENTS: CAPRYLYL GLYCOL; SODIUM POLYACRYLATE (2500000 MW); PHENOXYETHANOL; .ALPHA.-TOCOPHEROL ACETATE; DIMETHICONE; PEG-100 STEARATE; CHLORPHENESIN; WATER; SILICON DIOXIDE; GLYCERYL STEARATE; ALOE BARBADENSIS LEAF; GLYCERIN

Active Ingredients

Avobenzone 2.7%, Homosalate 4.0%, Octisalate 4.0%, Octocrylene 5.0%

Purpose

Sunscreen

Uses

■ helps prevent sunburn ■ if used as directed with other sun protection measures (see Directions), decreases the risk of skin cancer and early aging caused by the sun.

Warnings

For external use only.
May stain some fabrics.

Do not use

■ on damaged or broken skin.

When using this product

■ keep out of eyes. Rinse with water to remove.

Stop use and ask a doctor if

■ rash occurs.

Keep out of reach of children.

If product is swallowed, get medical help or contact a Poison Control Center right away.

Directions

■ apply liberally 15 minutes before sun exposure ■ reapply: ■ after 80 minutes of swimming or sweating ■ immediately after towel drying ■ at least every 2 hours ■ S un Protection Measures. Spending time in the sun increases your risk of skin cancer and early skin aging. To decrease this risk, regularly use a sunscreen with a broad spectrum SPF value of 15 or higher and other sun protection measures including: ■ limit time in the sun, especially from 10 a.m.–2 p.m. ■ wear long-sleeved shirts, pants, hats, and sunglasses ■ children under 6 months: Ask a doctor

Other Information

■ protect the product in this container from excessive heat and direct sun

Inactive Ingredients:

Water, Glycerin, Dimethicone,Silica, Phenoxyethanol, Acrylates/C12‐22 Alkyl Methacrylate Copolymer, Caprylyl Glycol, Sodium Polyacrylate, Chlorphenesin, Disodium EDTA, Glyceryl Stearate, PEG‐100 Stearate, Tocopheryl Acetate, Aloe Barbadensis Leaf Juice.

Questions or comments?

Call 1-800-SafeSun, Mon-Fri

Principle Display Panel

New

BANANA BOAT

Sheer

Sensitive

FACE

SUNSCREEN LOTION

UVA/UVB BROAD SPECTRUM SPF 50

50

Dermatologist

& Pediatrician

APPROVED

Water Resistant (80 minutes)

FRAGRANCE &

ALCOHOL FREE*

*no ethanol/ethnyl alcohol

3 FL.OZ. (88mL)